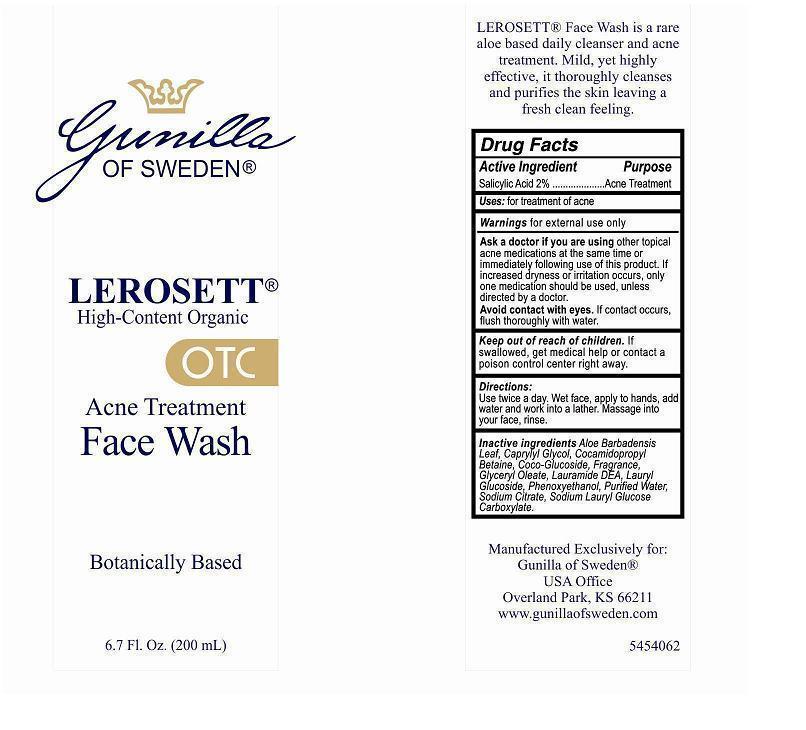 DRUG LABEL: LEROSETT High-Content Organic Acne Treatment
NDC: 58133-062 | Form: GEL
Manufacturer: Cosmetic Specialty labs, Inc.
Category: otc | Type: HUMAN OTC DRUG LABEL
Date: 20130124

ACTIVE INGREDIENTS: SALICYLIC ACID 2 g/100 mL
INACTIVE INGREDIENTS: ALOE VERA LEAF; CAPRYLYL GLYCOL; COCAMIDOPROPYL BETAINE; COCO GLUCOSIDE; GLYCERYL OLEATE; LAURIC DIETHANOLAMIDE; LAURYL GLUCOSIDE; PHENOXYETHANOL; WATER; SODIUM CITRATE; SODIUM LAURYL GLYCOL CARBOXYLATE

ACTIVE INGREDIENT

Salicylic Acid 2%

PURPOSE

Acne Treatment

KEEP OUT OF REACH OF CHILDREN

If swallowed, get medical help or contact a poison control center right away.

USES

for treatment of acne

WARNINGS

for external use only

Ask a doctor if you are using other topical acne medications at the same time or immediately following use of this product. If increased dryness or irrritation occurs, only one medication should be used, unless directed by a doctor.

Avoid contact with eyes. If contact occurs, flush thoroughly with water.

DIRECTIONS

Use twice a day. Wet face, apply to hands, add water and work: into a lather. Massage into your face, rinse.

INACTIVE INGREDIENTS

Aloe Barbadensis Leaf, Caprylyl GIycol, Cocamidopropyl Betaine, Coco-Glucoside, Fragrance, Glyceryl Oleate, Lauramide DEA, Lauryl Glucoside, Phenoxyethanol, Purified Water, Sodium Citrate, Sodium Lauryl Glucose Carboxylate.